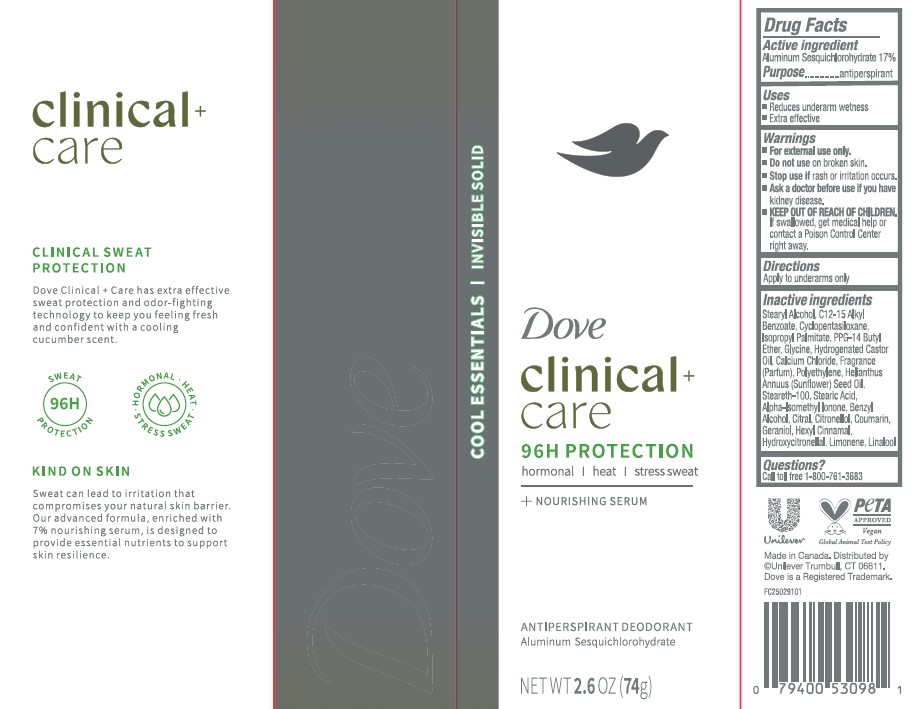 DRUG LABEL: Dove
NDC: 64942-2384 | Form: STICK
Manufacturer: Conopco Inc. d/b/a/ Unilever
Category: otc | Type: HUMAN OTC DRUG LABEL
Date: 20260211

ACTIVE INGREDIENTS: ALUMINUM SESQUICHLOROHYDRATE 17 g/100 g
INACTIVE INGREDIENTS: HEXYL CINNAMAL; ISOPROPYL PALMITATE; CITRONELLOL; GLYCINE; HELIANTHUS ANNUUS (SUNFLOWER) SEED OIL; STEARETH-100; CALCIUM CHLORIDE; LIMONENE, (+)-; STEARYL ALCOHOL; HYDROGENATED CASTOR OIL; POLYETHYLENE; PPG-14 BUTYL ETHER; BENZYL ALCOHOL; CITRAL; C12-15 ALKYL BENZOATE; ALPHA-ISOMETHYL IONONE; COUMARIN; HYDROXYCITRONELLOL; LINALOOL; CYCLOPENTASILOXANE; STEARIC ACID; GERANIOL

Dove Clinical + Care 96H Protection Cool Essentials Invisible Solid Antiperspirant Deodorant

DESCRIPTION

Dove Clinical + Care 96H Protection Cool Essentials Invisible Solid Antiperspirant Deodorant

ACTIVE INGREDIENT

Aluminum Sesquichlorohydrate 17%

PURPOSE

Antiperspirant

INDICATIONS AND USAGE

Reduces underarm wetness
Extra effective

WARNINGS

For external use only.
• Do not use on broken skin.• Stop use if rash or irritation occurs. • Ask a doctor before
use if you have kidney disease

Keep out of reach of children. If swallowed,get medical help or contact a Poison Control Center right away.

DOSAGE AND ADMINISTRATION

Apply to underarms only

INACTIVE INGREDIENT

Stearyl Alcohol, C12-15 Alkyl Benzoate, Cyclopentasiloxane, Isopropyl Palmitate, PPG-14 Butyl Ether, Glycine, Hydrogenated Castor Oil,Calcium Chloride, Polyethylene, Helianthus Annuus (Sunflower) Seed Oil, Steareth-100, Stearic Acid, Alpha-Isomethyl Ionone, Benzyl Alcohol, Citral, Citronellol, Coumarin, Geraniol, Hexyl Cinnamal, Hydroxycitronellol, Limonene, Linalool

QUESTIONS

call 1-800-761-3683